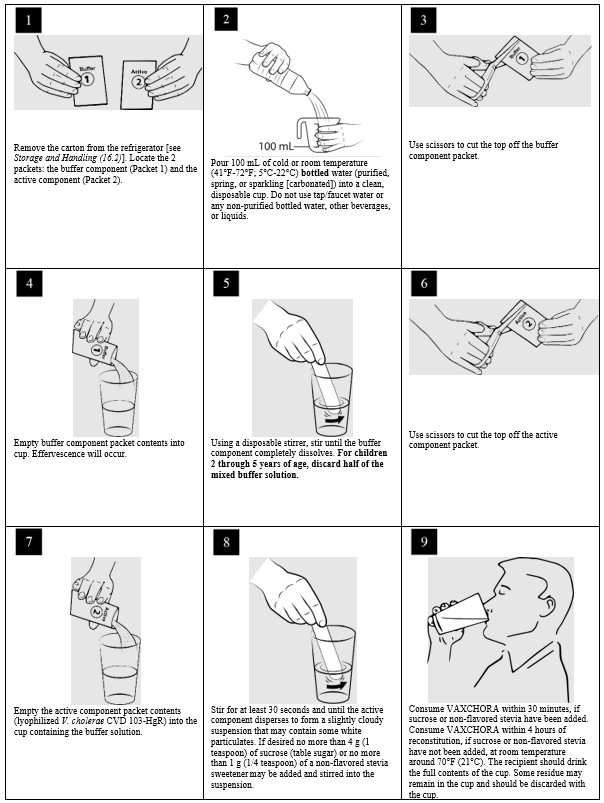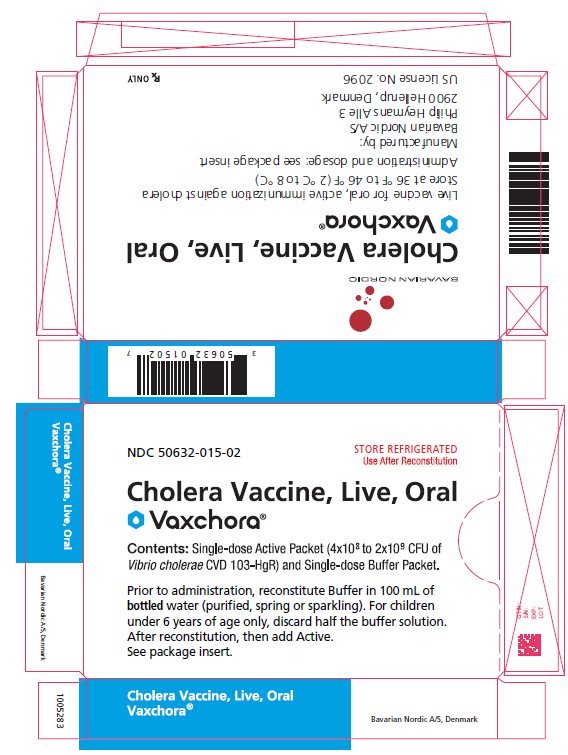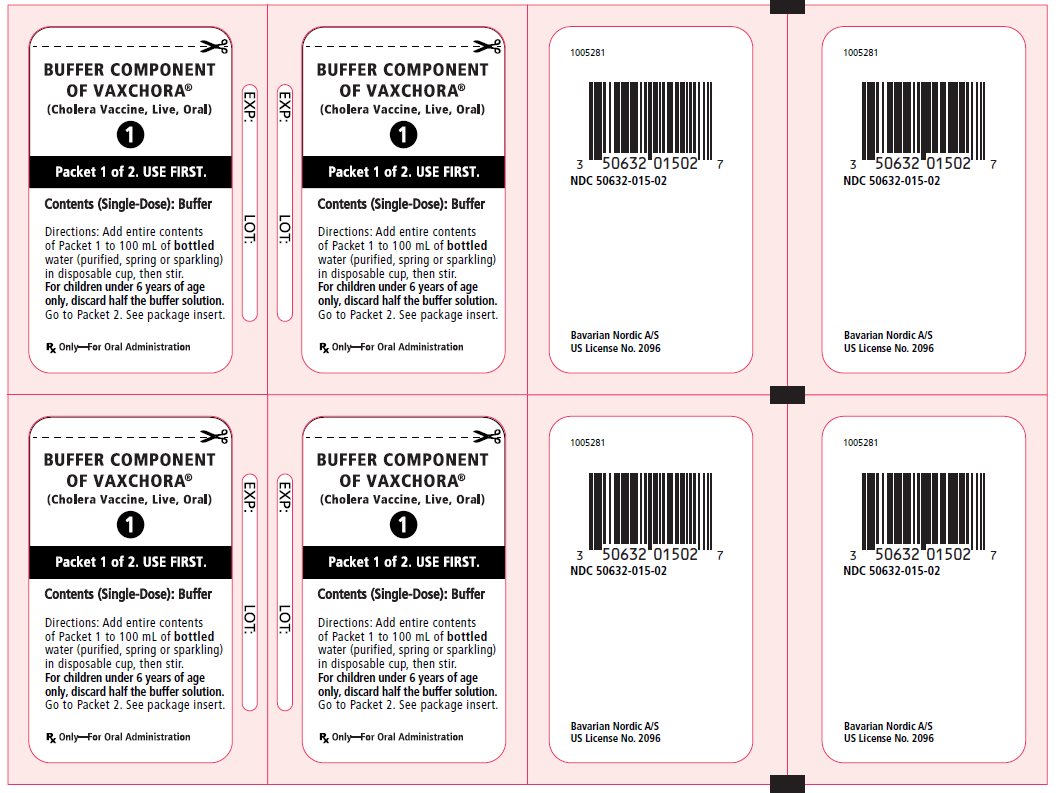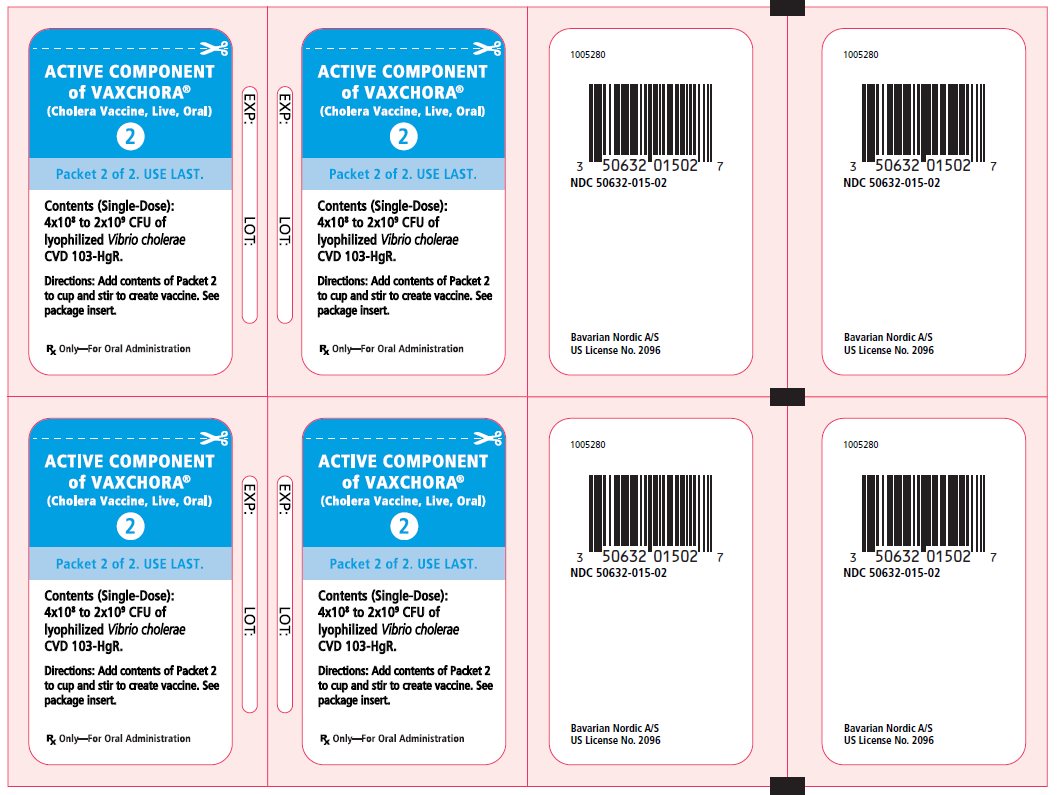 DRUG LABEL: Vaxchora
NDC: 50632-015 | Form: KIT | Route: ORAL
Manufacturer: Bavarian Nordic A/S
Category: other | Type: VACCINE LABEL
Date: 20250207

ACTIVE INGREDIENTS: VIBRIO CHOLERAE CVD 103-HGR STRAIN LIVE ANTIGEN 1200000000 [CFU]/1 1
INACTIVE INGREDIENTS: SUCROSE; HYDROLYZED CASEIN (ENZYMATIC; 1000 MW); ASCORBIC ACID; ANHYDROUS LACTOSE; SODIUM BICARBONATE; SODIUM CARBONATE; ASCORBIC ACID; ANHYDROUS LACTOSE

HIGHLIGHTS OF PRESCRIBING INFORMATION

These highlights do not include all the information needed to use VAXCHORA safely and effectively. See full prescribing information for VAXCHORA.
VAXCHORA® (Cholera Vaccine, Live, Oral)
Suspension for Oral Administration
Initial U.S. Approval: 2016

1 INDICATIONS AND USAGE

VAXCHORA is a vaccine indicated for active immunization against disease caused by Vibrio cholerae serogroup O1. VAXCHORA is approved for use in persons 2 through 64 years of age traveling to cholera-affected areas. (1)

Limitations of Use:

- The effectiveness of VAXCHORA has not been established in persons living in cholera-affected areas. (1.1)
- The effectiveness of VAXCHORA has not been established in persons who have pre-existing immunity due to previous exposure to V. cholerae or receipt of a cholera vaccine. (1.1)
- VAXCHORA has not been shown to protect against disease caused by V. cholerae serogroup O139 or other non-O1 serogroups. (1.1)

2 DOSAGE AND ADMINISTRATION

- For oral administration only.
- Prepare and administer VAXCHORA in a healthcare setting equipped to dispose of medical waste. (2.3)
- Prepare VAXCHORA by reconstituting the buffer component in 100 milliliters (mL) of bottled water (purified, spring, or sparkling [carbonated]); for children 2 through 5 years of age, discard half the reconstituted buffer solution; then add the active component (lyophilized V. cholerae CVD 103-HgR). (2.3) After preparation, a single dose of VAXCHORA is 100 mL for persons 6 through 64 years or 50 mL for children 2 through 5 years of age. (3)
- Instruct recipients to avoid eating or drinking for 60 minutes before and after oral ingestion of VAXCHORA. (2.2)
- Administer VAXCHORA a minimum of 10 days before potential exposure to cholera. (2.1)

3 DOSAGE FORMS AND STRENGTHS

Suspension for oral administration supplied as a packet of the buffer component and a packet of the active component (lyophilized V. cholerae CVD 103-HgR). After preparation, a single dose of VAXCHORA is 100 mL for persons 6 years through 64 years of age or 50 mL for children 2 through 5 years of age. (3)

4 CONTRAINDICATIONS

Severe allergic reaction (e.g., anaphylaxis) to any ingredient of VAXCHORA or to a previous dose of any cholera vaccine. (4)

5 WARNINGS AND PRECAUTIONS

- The safety and effectiveness of VAXCHORA have not been established in immunocompromised persons. (5.1)
- VAXCHORA may be shed in the stool of recipients for at least 7 days. There is a potential for transmission of the vaccine strain to non-vaccinated close contacts (e.g., household contacts). Use caution when considering whether to administer VAXCHORA to individuals with immunocompromised close contacts. (5.2)

6 ADVERSE REACTIONS

The most common adverse reactions for adults (incidence > 3%) were tiredness (31%), headache (29%), abdominal pain (19%), nausea/vomiting (18%), lack of appetite (17%) and diarrhea (4%). (6)

The most common adverse reactions for children and adolescents (incidence ≥10%) were:

- Age 12 to <18 years: headache (45%), tiredness (41%), abdominal pain (38%), lack of appetite (29%) and nausea (22%).
- Age 6 to <12 years: tiredness (35%), abdominal pain (27%), headache (26%), lack of appetite (15%) and nausea (14%).
- Age 2 to <6 years: tiredness (31%), loss of appetite (19%), and abdominal pain (17%). (6)

To report SUSPECTED ADVERSE REACTIONS, contact Bavarian Nordic A/S at 1-833-365-9596 or VAERS at 1-800-822-7967 or www.vaers.hhs.gov.

7 DRUG INTERACTIONS

Avoid concomitant administration of VAXCHORA with systemic antibiotics since these agents may be active against the vaccine strain. Do not administer VAXCHORA to patients who have received oral or parenteral antibiotics within 14 days prior to vaccination. (7.2)

Immune responses to VAXCHORA may be diminished when VAXCHORA is administered concomitantly with chloroquine. Administer VAXCHORA at least 10 days before beginning antimalarial prophylaxis with chloroquine. (7.2)

FULL PRESCRIBING INFORMATION

1 INDICATIONS AND USAGE

VAXCHORA is a vaccine indicated for active immunization against disease caused by Vibrio cholerae serogroup O1 in persons 2 through 64 years of age traveling to cholera-affected areas.

1.1 Limitations of Use

The effectiveness of VAXCHORA has not been established in persons living in cholera-affected areas.

The effectiveness of VAXCHORA has not been established in persons who have pre-existing immunity due to previous exposure to V. cholerae or receipt of a cholera vaccine.

VAXCHORA has not been shown to protect against disease caused by V. cholerae serogroup O139 or other non-O1 serogroups.

2 DOSAGE AND ADMINISTRATION

For oral administration only.

2.1 Dose and Schedule

Administer a single oral dose of VAXCHORA a minimum of 10 days before potential exposure to cholera.

The safety and effectiveness of revaccination with VAXCHORA have not been established.

2.2 Restrictions on Eating and Drinking

Instruct recipients to avoid eating or drinking for 60 minutes before and after oral ingestion of VAXCHORA.

2.3 Preparation, Reconstitution and Administration

Prepare and administer VAXCHORA in a healthcare setting equipped to dispose of medical waste [see Disposal Instructions (2.4)].

1. Remove the carton from the refrigerator [see Storage and Handling (16.2)]. Locate the 2 packets: the buffer component (Packet 1) and the active component (Packet 2).
2. Pour 100 milliliters (mL) of cold or room temperature (41°F-72°F; 5°C-22°C) bottled water (purified, spring, or sparkling [carbonated]) into a clean, disposable cup. Do not use tap/faucet water, or any non-purified bottled water, other beverages, or liquids.
3. Use scissors to cut the top off the buffer component packet.
4. Empty buffer component packet contents into cup. Effervescence will occur.
5. Using a disposable stirrer, stir until the buffer component completely dissolves. For children 2 through 5 years of age, discard half of the buffer solution after mixing.
6. Use scissors to cut the top off the active component packet.
7. Empty the active component packet contents (lyophilized V. cholerae CVD 103-HgR) into the cup containing the buffer solution.
8. Stir for at least 30 seconds and until active component disperses to form a slightly cloudy suspension that may contain some white particulates.
  If desired, no more than 4 g (1 teaspoon) of sucrose (table sugar) or no more than 1 g (1/4 teaspoon) of non-flavored stevia sweeteners may be added and stirred into the suspension. Do not add any other sweeteners or medicinal flavorings as this can reduce the effectiveness of the vaccine.
9. Consume VAXCHORA within 30 minutes, if sucrose or non-flavored stevia are added. Consume VAXCHORA within 4 hours of reconstitution, if sucrose and non-flavored stevia have not been added, at room temperature around 70 °F (21°C).
  The recipient should drink the full contents of the cup. Some residue may remain in the cup and should be discarded with the cup.

NOTE: If the packets are reconstituted in the improper order, the vaccine must be discarded [see Disposal Instructions (2.4)].

2.4 Disposal Instructions

Dispose of the cup, packets, and stirrer according to standard procedures for medical waste.

Inactivate any spilled vaccine and clean any non-disposable equipment used in the preparation of VAXCHORA with 70% isopropyl alcohol or 10% bleach solution.

3 DOSAGE FORMS AND STRENGTHS

VAXCHORA is a suspension for oral administration. Before reconstitution, each dose of VAXCHORA is supplied as a foil packet of buffer and an accompanying foil packet of the active component (lyophilized V. cholerae CVD 103-HgR). After reconstitution, a single dose of VAXCHORA is 100 mL (50 mL for children 2 through 5 years of age).

4 CONTRAINDICATIONS

Do not use in persons who have a history of severe allergic reaction (e.g., anaphylaxis) to any ingredient of VAXCHORA or to a previous dose of any cholera vaccine [see Description (11)].

5 WARNINGS AND PRECAUTIONS

5.1 Altered Immunocompetence

The safety and effectiveness of VAXCHORA have not been established in immunocompromised persons [see Immunocompromised Individuals (8.6)].

5.2 Shedding and Transmission

VAXCHORA may be shed in the stool of recipients for at least 7 days. There is a potential for transmission of the vaccine strain to non-vaccinated close contacts (e.g., household contacts) [see Pharmacodynamics (12.2)]. Use caution when considering whether to administer VAXCHORA to individuals with immunocompromised close contacts.

6 ADVERSE REACTIONS

Because clinical trials are conducted under widely varying conditions, adverse reaction rates observed in clinical trials of a vaccine cannot be directly compared to rates in the clinical trials of another vaccine and may not reflect the rates observed in practice.

The most common adverse reactions for adults (incidence > 3%) were tiredness (31%), headache (29%), abdominal pain (19%), nausea/vomiting (18%), lack of appetite (17%) and diarrhea (4%).

The most common adverse reactions for children and adolescents (incidence ≥10%) were:

- Cohort 1 - age 12 to <18 years: headache (45%), tiredness (41%), abdominal pain (38%), lack of appetite (29%) and nausea (22%).
- Cohort 2 - age 6 to <12 years: tiredness (35%), abdominal pain (27%), headache (26%), lack of appetite (15%) and nausea (14%).
- Cohort 3 - age 2 to <6 years: tiredness (31%), lack of appetite (19%), and abdominal pain (17%).

6.1 Clinical Trials Experience

Trials in Adults

The safety of VAXCHORA was evaluated in four randomized, placebo-controlled, multicenter clinical trials. A total of 3235 adults 18 through 64 years of age received one dose of VAXCHORA and 562 received placebo [physiologic saline (N=551) or lactose (N=11)]. Overall, the mean age was 32.5 years; 53.8% of trial participants were female; 67.1% were White, 27.3% were Black or African American, 1.8% were Asian, 1.7% were multiracial, 1.3% were other, 0.6% were American Indian or Alaskan Native and 0.3% were Native Hawaiian or Pacific Islander. There were 9.3% Hispanic or Latino participants.

Solicited Adverse Reactions

Adults 18 through 45 years of age received VAXCHORA in a multi-center, double-blind, randomized (8:1), placebo-controlled trial conducted in the United States and Australia (Study 1). The safety analysis set included 2789 VAXCHORA recipients. Solicited adverse reactions were recorded daily for 7 days following vaccination. Table 1 presents the frequency and severity of solicited adverse reactions observed within 7 days following receipt of VAXCHORA or placebo in Study 1.

Table 1: Rates of Solicited Adverse Reactions Reported in VAXCHORA Trial Participants 18 to 45 Years of Age During 7 Days Post-Vaccination − Study 1a
Adverse Reaction | VAXCHORA (N=2789)b % | Placebo (Saline) (N=350)b %
Tiredness | 31.3 | 27.4
Mild | 18.7 | 16.3
Moderate | 12.0 | 9.9
Severe | 0.7 | 1.2
Potentially life-threatening | 0.0 | 0.0
Headache | 28.9 | 23.6
Mild | 18.9 | 14.6
Moderate | 9.6 | 8.8
Severe | 0.5 | 0.3
Potentially life-threatening | 0.0 | 0.0
Abdominal Pain | 18.7 | 16.9
Mild | 12.1 | 12.0
Moderate | 6.2 | 5.0
Severe | 0.4 | 0.0
Potentially life-threatening | 0.0 | 0.0
Nausea/Vomiting | 18.3 | 15.2
Mild | 13.3 | 11.4
Moderate | 4.7 | 3.8
Severe | 0.3 | 0.0
Potentially life-threatening | 0.0 | 0.0
Lack of Appetite | 16.5 | 16.6
Mild | 11.7 | 12.2
Moderate | 4.4 | 4.4
Severe | 0.3 | 0.0
Potentially life-threatening | 0.0 | 0.0
Diarrhea | 3.9 | 1.2
Mild | 2.4 | 0.9
Moderate | 0.7 | 0.3
Severe | 0.8 | 0.0
Potentially life-threatening | 0.04 | 0.0
Fever | 0.6 | 1.2
Mild | 0.2 | 0.3
Moderate | 0.3 | 0.9
Severe | 0.07 | 0.0
Potentially life-threatening | 0.04 | 0.0
a Data are derived from Study 1 (NCT02094586).
b N represents number of subjects who completed a memory aid.
Grading scales are defined as follows:
Tiredness, Headache, Abdominal Pain, Nausea, Lack of Appetite: Mild = no interference with activity, Moderate = Some interference with activity, Severe = significant, prevents daily activity, Potentially Life Threatening = emergency room (ER) visit or hospitalization.
Vomiting: Mild = 1-2 episodes/24 hours, Moderate = >2 episodes/24 hours, Severe = requires intravenous hydration, Potentially Life Threatening = ER visit or hospitalization for hypotensive shock.
Diarrhea: Mild = 4 loose stools/24 hours, Moderate = 5 loose stools/24 hours, Severe = ≥6 loose stools /24 hours, Potentially Life Threatening = ER visit or hospitalization.
Fever: Mild = 38.0-38.4ºC/100.4-101.1ºF, Moderate = 38.5-38.9ºC/101.2-102.0ºF, Severe = 39.0‑40.0ºC/102.1-104.0ºF, Potentially Life Threatening = >40.0 ºC/104.0 ºF.

Serious Adverse Events

In a pooled analysis of the four clinical studies, 0.6% (20/3235) of VAXCHORA recipients and 0.5% (3/562) of placebo recipients reported a serious adverse event within 6 months post-vaccination. None of these events were considered to be related to vaccination.

Pediatric Trial

The safety of VAXCHORA in children was evaluated in one randomized, placebo-controlled, multicenter clinical trial. A total of 468 children 2 through 17 years of age received one dose of VAXCHORA and 75 received placebo (physiologic saline). The mean age was 9.0 years; 51.6% were male; 59.5% were White, 31.3% were Black, 7.7% were multiracial, 0.9% were Asian, and 0.6% were American Indian/Alaskan Native. There were 8.7% Hispanic or Latino participants.

Solicited Adverse Reactions

Children 2 through 17 years of age received VAXCHORA in a multi-center, double-blind, randomized (6:1), placebo-controlled trial conducted in the United States (Study 5). Randomization was stratified by age, and children were enrolled in three separate age cohorts: 12 to < 18 years (Cohort 1), 6 to < 12 years (Cohort 2), and 2 to < 6 years (Cohort 3). The safety analysis set included 468 VAXCHORA recipients and 75 placebo recipients. Solicited adverse reactions were recorded daily for 7 days following vaccination. Table 2 presents the frequency and severity of solicited adverse reactions observed within 7 days following receipt of VAXCHORA or placebo in Study 5 for the 3 study cohorts.

Table 2: Rates of Solicited Adverse Reactions Reported in VAXCHORA Pediatric Trial (Study 5) Participants 2 to 17 Years of Age During 7 Days Post-Vaccination by Age cohort
Adverse Reaction | Cohort 1 Ages 12 to <18 years VAXCHORA (N=165)b % | Cohort 1 Ages 12 to <18 years Placebo (Saline) (N=24)b % | Cohort 2 Ages 6 to <12 years VAXCHORA (N=157)b % | Cohort 2 Ages 6 to <12 years Placebo (Saline) (N=25)b % | Cohort 3 Ages 2 to <6 years VAXCHORA (N=146)b % | Cohort 3 Ages 2 to <6 years Placebo (Saline) (N=26)b %
Tiredness | 40.6 | 37.5 | 35.0 | 32.0 | 30.8 | 23.1
Mild | 31.5 | 33.3 | 22.3 | 20.0 | 19.2 | 15.4
Moderate | 8.5 | 0.0 | 12.1 | 12.0 | 11.6 | 7.7
Severe | 0.6 c | 4.2 | 0.6 | 0.0 | 0.0 | 0
Headache | 44.8 | 45.8 | 26.1 | 24.0 | 8.9 | 7.7
Mild | 34.5 | 45.8 | 19.1 | 20.0 | 6.8 | 3.8
Moderate | 9.7 | 0.0 | 5.7 | 4.0 | 2.1 | 3.8
Severe | 0.6 | 0.0 | 1.3 | 0.0 | 0.0 | 0.0
Abdominal Pain | 37.6 | 16.7 | 27.4 | 24.0 | 17.1 | 15.4
Mild | 28.5 | 12.5 | 23.6 | 16.0 | 14.4 | 15.4
Moderate | 8.5 | 4.2 | 3.8 | 8.0 | 2.7 | 0.0
Severe | 0.6 | 0.0 | 0.0 | 0.0 | 0.0 | 0.0
Lack of Appetite | 29.1 | 12.5 | 15.3 | 20.0 | 19.2 | 11.5
Mild | 23.6 | 12.5 | 12.7 | 16.0 | 12.3 | 7.7
Moderate | 5.5 | 0.0 | 1.9 | 4.0 | 6.8 | 3.8
Severe | 0.0 | 0.0 | 0.6 | 0.0 | 0.0 | 0.0
Nausea | 22.4 | 25.0 | 14.0 | 16.0 | 6.8 | 15.4
Mild | 17.0 | 20.8 | 12.1 | 8.0 | 6.2 | 15.4
Moderate | 4.8 | 4.2 | 1.9 | 8.0 | 0.7 | 0.0
Severe | 0.6 | 0.0 | 0.0 | 0.0 | 0.0 | 0.0
Vomiting | 5.5 | 0.0 | 4.5 | 0.0 | 1.4 | 11.5
Mild | 3.6 | 0.0 | 2.5 | 0.0 | 1.4 | 7.7
Moderate | 1.2 | 0.0 | 1.9 | 0.0 | 0.0 | 3.8
Severe | 0.6 | 0.0 | 0.0 | 0.0 | 0.0 | 0.0
Fever | 1.2 | 0.0 | 3.2 | 4.0 | 2.1 | 3.8
Mild | 0.6 | 0.0 | 0.0 | 0.0 | 0.7 | 0.0
Moderate | 0.0 | 0.0 | 0.6 | 4.0 | 0.7 | 0.0
Severe | 0.6 | 0.0 | 2.5 | 0.0 | 0.7 d | 3.8
Diarrhea | 3.6 | 4.2 | 0.0 | 0.0 | 0.7 | 0.0
Mild | 1.8 | 0.0 | 0.0 | 0.0 | 0.7 | 0.0
Moderate | 0.0 | 4.2 | 0.0 | 0.0 | 0.0 | 0.0
Severe | 1.8 | 0.0 | 0.0 | 0.0 | 0.0 | 0.0
a Data are derived from Study 5 (NCT03220737).
b N represents number of subjects with a completed a memory aid.
c Includes 1 case evaluated in the emergency room for an associated viral pharyngitis considered not related to vaccination.
d Includes 1 case with temperature greater than 40°C considered not related to vaccination
Pediatric Grading scales are defined as follows:
Tiredness, Headache, Abdominal Pain, Nausea, Lack of Appetite: Mild = no interference with activity, Moderate = Some interference with activity, Severe = significant, prevents daily activity, Potentially Life Threatening = emergency room (ER) visit or hospitalization.
Vomiting: Mild = 1-2 episodes/24 hours, Moderate = >2 episodes/24 hours, Severe = requires intravenous hydration, Potentially Life Threatening = ER visit or hospitalization for hypotensive shock.
Diarrhea: Mild = 4 loose stools/24 hours, Moderate = 5 loose stools/24 hours, Severe = ≥6 loose stools /24 hours, Potentially Life Threatening = ER visit or hospitalization.
Fever: Mild = 38.0-38.4ºC/100.4-101.1ºF, Moderate = 38.5-38.9ºC/101.2-102.0ºF, Severe = 39.0‑40.0ºC/102.1-104.0ºF, Potentially Life Threatening = >40.0 ºC/104.0 ºF.

In total, 13.2% of VAXCHORA recipients reported an unsolicited adverse event that was considered related to study treatment, compared to 9.3% for placebo recipients.

The most frequent unsolicited adverse event for VAXCHORA was loose stool in Cohort 1 (13.9%), Cohort 2 (11.5%) and Cohort 3 (5.5%).

Serious Adverse Events

In Study 5, 0.2% (1/468) of VAXCHORA recipients and 1.3% (1/75) of placebo recipients reported a serious adverse event within 6 months post-vaccination. None of these events were considered to be related to vaccination.

7 DRUG INTERACTIONS

7.1 Food and Drink

Avoid food or drink for 60 minutes before and after vaccine administration [see Restrictions on Eating and Drinking (2.2)].

7.2 Concomitant Vaccines or Medications

Vaccines

No data are available on concomitant administration of VAXCHORA with other vaccines.

Antibiotics

Avoid concomitant administration of VAXCHORA with systemic antibiotics since these agents may be active against the vaccine strain and prevent a sufficient degree of multiplication to occur in order to induce a protective immune response. Do not administer VAXCHORA to patients who have received oral or parenteral antibiotics within 14 days prior to vaccination.

Antimalarial Prophylaxis

Data from a study with a similar product indicate that the immune responses to VAXCHORA may be diminished when VAXCHORA is administered concomitantly with chloroquine. Administer VAXCHORA at least 10 days before beginning antimalarial prophylaxis with chloroquine.

7.3 Immunosuppressive Treatments

Immunosuppressive therapies, including irradiation, antimetabolites, alkylating agents, cytotoxic drugs and corticosteroids (used in greater than physiologic doses), may reduce the immune response to VAXCHORA [see Use in Specific Populations (8.6)].

8 USE IN SPECIFIC POPULATIONS

8.1 Pregnancy

Risk Summary

VAXCHORA is not absorbed systemically following oral administration, and maternal use is not expected to result in fetal exposure to the drug.

Clinical Considerations

Disease-associated maternal and/or embryo/fetal risk

Maternal cholera disease is associated with adverse pregnancy outcomes including fetal death.

Fetal/neonatal adverse reactions

The vaccine strain may be shed in the stool of the vaccinated mother for at least 7 days, with a potential for transmission of the vaccine strain from mother to infant during vaginal delivery.

8.2 Lactation

Risk Summary

VAXCHORA is not absorbed systemically by the mother following oral administration, and breastfeeding is not expected to result in exposure of the child to VAXCHORA.

8.4 Pediatric Use

The safety and effectiveness of VAXCHORA have not been established in children younger than 2 years of age.

8.5 Geriatric Use

The safety and effectiveness of VAXCHORA have not been established in adults 65 years of age or older.

8.6 Immunocompromised Individuals

The safety and effectiveness of VAXCHORA have not been established in immunocompromised individuals. The immunologic response to VAXCHORA may be diminished in immunocompromised individuals [see Drug Interactions (7.3)].

11 DESCRIPTION

VAXCHORA (Cholera Vaccine, Live, Oral) is a live, attenuated bacterial vaccine suspension for oral administration containing the V. cholerae strain CVD 103-HgR. CVD 103-HgR was constructed from the serogroup O1 classical Inaba strain 569B by deleting the catalytic domain sequence of both copies of the ctxA gene, which prevents the synthesis of active cholera toxin (CT). This attenuated strain remains able to synthesize the immunogenic non-toxic B subunit of CT (encoded by the ctxB gene). In addition, a marker was inserted into the hemolysin gene locus (hlyA) to enable differentiation of the vaccine strain from wild type V. cholerae O1.

The vaccine strain is grown in fermentors under controlled conditions in medium containing casamino acids, yeast extract, mineral salts, and an anti-foaming agent. The bacteria are concentrated by ultrafiltration before addition of a stabilization solution containing ascorbic acid (an antioxidant), Hy-Case SF (hydrolyzed casein [a protein derived from cow's milk], a cryoprotectant), and sucrose (a cryoprotectant). The stabilized bacteria are lyophilized, milled, and blended with anhydrous lactose (a bulking agent). The active component blend is filled into packets.

The buffer component is manufactured by blending together sodium bicarbonate (a gastric acid neutralizer), sodium carbonate (a buffer), ascorbic acid (a buffer and water chlorine neutralizer), and anhydrous lactose (a manufacturing flow aid). The buffer component blend is filled into packets. One buffer component packet and one active component packet are packaged into individual single dose cartons for distribution.

After reconstitution, VAXCHORA contains 4 x 10^8 to 2 x 10^9 colony forming units (CFU) of live attenuated V. cholerae CVD 103-HgR. The resulting suspension should be slightly cloudy and may contain white particulates. The active and buffer ingredients are shown in Table 3.

Table 3: Vaccine Composition
Active Component Packet; Ingredient | Active Component Packet; Quantity/packet
V. cholerae CVD 103-HgR | 4 x 10^8 to 2 x 10^9 CFUa
Sucrose | ≤ 165.37 mgb
Hy-Case SF (hydrolyzed casein) | ≤ 17.11 mg
Ascorbic acid | ≤ 8.55 mg
Anhydrous lactose | ≤ 2.09 gc
Buffer Component Packet; Ingredient | Buffer Component Packet; Quantity/packet
Sodium bicarbonate | 2.16–2.41 g
Sodium carbonate | 0.24-0.49 g
Ascorbic acid | 1.50–1.80 g
Anhydrous lactose | 0.18–0.22 g
a CFU=colony forming units.
b mg=milligrams.
c g=grams.

12 CLINICAL PHARMACOLOGY

12.1 Mechanism of Action

VAXCHORA contains live attenuated cholera bacteria that replicate in the gastrointestinal tract of the recipient. Immune mechanisms conferring protection against cholera following receipt of VAXCHORA have not been determined. However, rises in serum vibriocidal antibody 10 days after vaccination with VAXCHORA were associated with protection in a human challenge study (Study 2) [see Immunogenicity (14.2)].

12.2 Pharmacodynamics

Shedding of the vaccine strain was evaluated in the first 7 days post-vaccination in a study of 53 healthy adult vaccine recipients (Study 3). VAXCHORA was shed in the stools of 11.3% [95% CI 4.3%, 23.0%] of vaccine recipients on any day through 7 days post-vaccination. During the 7 days post-vaccination, the proportion of subjects shedding was highest on day 7 (7.5% [95% CI 2.1%, 18.2%]). The duration of shedding of the vaccine strain is unknown.

13 NONCLINICAL TOXICOLOGY

13.1 Carcinogenesis, Mutagenesis, Impairment of Fertility

VAXCHORA has not been evaluated for the potential to cause carcinogenicity or genotoxicity, or to impair fertility.

14 CLINICAL STUDIES

14.1 Efficacy Against V. cholerae Challenge

Study 2 was a randomized, double-blind, saline placebo-controlled V. cholerae challenge study conducted in the US. Subjects 18 through 45 years of age (N=197) with no prior history of cholera infection or travel to a cholera-endemic area in the previous 5 years were randomized according to a 1:1 ratio to receive one dose of VAXCHORA or placebo. In order to identify the subset of subjects to be challenged, an unblinded statistician prepared four randomly ordered lists of subjects per site, one list each for vaccine recipients with blood type O, vaccine recipients with non-O blood types, placebo recipients with blood type O, and placebo recipients with non-O blood types. This was done to maintain a minimum of 60% blood group O subjects in each treatment group. Individuals with type O blood are less likely to be infected with V. cholerae, but are at risk for developing severe cholera if infected. Each site was provided with a blinded version of the four lists specific to its site and advised on the number of subjects from each list to challenge. In the event that a subject was determined to be ineligible for challenge, the site was instructed to select the next subject from the same list as the ineligible subject.

The challenges were split into 2 cohorts for 10 day and 3 month challenges. Subjects were admitted to an inpatient unit. Subjects had nothing by mouth from midnight before ingestion of the challenge strain, except for water, and had nothing by mouth for 90 minutes after ingestion of the challenge strain. Approximately 1 minute prior to challenge, subjects ingested 120 mL sodium bicarbonate (NaHCO3) buffer. The oral challenge consisted of 1 x 10^5 CFU live wild type V. cholerae El Tor Inaba N16961 in 30 mL NaHCO3 buffer at 10 days or 3 months post-vaccination. The co-primary objectives were to demonstrate the efficacy of a single dose of VAXCHORA in the prevention of moderate to severe diarrhea following challenge at 10 days and 3 months post-vaccination. Moderate to severe diarrhea was defined as cumulative diarrheal purge ≥ 3 liters (L) within 10 days after challenge. Diarrheal stool was defined as ≥ 2 unformed stools (takes shape of container) collected during a 48 hour period ≥ 200 grams (g) or a single unformed stool ≥ 300 g. Subjects were instructed to collect every stool from the time of challenge until discharge from the inpatient unit. Nursing staff or study personnel inspected all stool, graded the consistency of the stool and calculated the total weight of diarrheal stool per day. Weight of stool was converted to volume using the formula 1 g=1 mL. VAXCHORA recipients challenged at 10 days post-vaccination and VAXCHORA recipients challenged at 3 months post-vaccination were compared with a pooled group of placebo (saline) recipients challenged at 10 days or 3 months post-vaccination.

Of the 95 VAXCHORA recipients, 68 were challenged; 35 were challenged at 10 days post-vaccination and 33 were challenged at 3 months post-vaccination. Of the 102 placebo recipients, 66 were challenged; 33 were challenged at 10 days post-vaccination and 33 at 3 months post-vaccination. Among all randomized subjects, the mean age was 31.0 years. Overall, the mean age of the challenge population was 31.4 years. More males were in the vaccine group (71.6%) compared to the placebo group (54.9%). The majority of randomized subjects were Black (67.5%), 29.4% were White, 0.5% were American Indian/Alaskan Native, 0.5% were Asian, and 2.0% were other. There were 4.6% Hispanic or Latino participants. Overall 50.3% had blood type O. Among subjects selected for either challenge cohort, more males were challenged in the vaccine group (76.5%) compared to the placebo group (57.6%). The majority (70.9%) of the challenge population were Black, 25.4% were White, 0.7% were American Indian/Alaskan Native, 0.7% were Asian, and 2.2% were other. There were 3.7% Hispanic or Latino participants. Overall, 56.0% of challenged subjects had blood type O.

Vaccine efficacy against the occurrence of moderate to severe diarrhea at 10 days post-vaccination was 90.3% [95% CI 62.7%, 100.0%] and at 3 months post-vaccination was 79.5% [95% CI 49.9%, 100.0%] (Table 4).

Table 4: Vaccine Efficacy in the Prevention of Moderate to Severe Diarrhea Following Challenge with V. cholerae O1 El Tor Inaba at 10 Days and 3 Months Post-Vaccination (Intent-to-Treat Population)
Parameter | VAXCHORA 10 Day Challengea,c N=35d | VAXCHORA 3 Month Challengea,c N=33d | Combined Placeboa,b 10 Day or 3 Month Challengec N=66d
Number of Subjects with Moderate or Severe Diarrhea (Attack Rate)e | 2 (5.7%) | 4 (12.1%) | 39 (59.1%)
Vaccine Efficacy %f,g [95% CIh] | 90.3% [62.7%, 100.0%] | 79.5% [49.9%, 100.0%]
a Data are derived from Study 2 (NCT01895855).
b Combined placebo group comprised of all placebo recipients who were challenged at either 10 days (N=33) or 3 months (N=33) following vaccination.
c Challenge strain was V. cholerae O1 El Tor Inaba N16961.
d N=number of subjects challenged in each group.
e Moderate or severe diarrhea (≥ 3 liters of diarrhea) within 10 days after challenge.
f Vaccine Efficacy=[(Attack Rate in Placebo Group - Attack Rate in Vaccine Group)/Attack Rate in Placebo Group] x 100.
g Pre-specified criteria for success were that the lower bound of the two-sided 95% confidence interval for vaccine efficacy must be ≥30% in both the 10 Day and 3 Month challenge groups.
h CI=confidence interval.

14.2 Immunogenicity

Vibriocidal Antibody Against the Vaccine Strain (classical Inaba)

A vibriocidal antibody assay was used to measure serum levels of neutralizing antibodies against the vaccine strain.

Study 2 was a randomized, double-blind, saline placebo-controlled V. cholerae challenge study conducted in adults 18 through 45 years of age. In the subset of subjects challenged in Study 2, 91% [95% CI 82%, 97%] of vaccinees seroconverted prior to challenge and 9% developed moderate to severe cholera following challenge, while 2% of placebo recipients seroconverted prior to challenge and 59% developed moderate to severe cholera following challenge. Seroconversion was defined as a ≥ 4-fold rise in serum vibriocidal antibody from baseline to 10 days post vaccination. Based on the observed association between seroconversion and protection from V. cholerae disease, seroconversion rate at 10 days post-vaccination was used to evaluate response to vaccination in other age groups.

Study 1 was a randomized, double-blind, saline placebo-controlled safety and immunogenicity study conducted in the US and Australia. A total of 3146 subjects 18 through 45 years of age not previously exposed to cholera were randomized 8:1 to receive one dose of VAXCHORA or placebo. The mean age was 29.9 years; 45.2% were male; 68.3% were White, 25.6% were Black, 2.0% were Asian, 1.9% were multiracial, 1.4% were other, 0.4% were American Indian/Alaskan Native, and 0.3% were Native Hawaiian/Pacific Islander. There were 10.0% Hispanic or Latino participants.

In this study, classical Inaba vibriocidal antibody seroconversion rates were 93.5% [95% CI 92.5%, 94.4%] in vaccine recipients and 4% [95% CI 2%, 7%] in placebo recipients at 10 days post-vaccination.

Study 4 was a randomized, double-blind, placebo-controlled safety and immunogenicity study conducted in the US. A total of 398 subjects 46 through 64 years of age with no prior history of cholera infection or travel to a cholera-endemic area in the previous 5 years were randomized 3:1 to receive one dose of VAXCHORA or placebo. Overall, the mean age of the randomized population was 53.8 years; 45.7% were male; 74.9% were White, 21.9% were Black, 1.8% were American Indian/Alaskan Native, 0.5% were Asian, 0.5% were multiracial, 0.3% were Native Hawaiian/Pacific Islander, and 0.3% were other. There were 7.5% Hispanic or Latino participants.

Vibriocidal antibody seroconversion rates at 10 days post-vaccination for the classical Inaba strain among 46 through 64-year-old subjects in Study 4 were compared to those in 18 through 45-year-old subjects in Study 1. VAXCHORA recipients from Study 1 were in the same age group as those in Study 2, the V. cholerae challenge study.

Adults 46 through 64 years were shown to have a non-inferior rate of classical Inaba vibriocidal antibody seroconversion at 10 days post-vaccination compared to adults 18 through 45 years of age (Table 5).

Table 5: Vibriocidal Antibody Seroconversion Against Classical Inaba V. cholerae Vaccine Strain at 10 Days Post-Vaccination in Adults 46 through 64 Years of Age (Study 4) Compared to Adults 18 through 45 Years of Age (Study 1) [Bridging Analysis Population]
Study a | Dose/CFU | VAXCHORA Nb | VAXCHORA Seroconversion % [95% CIc]
Study 4 (46 through 64-year-olds) | 1 x 10^9 | 291 | 90.4% [86.4%, 93.5%]
Study 1 (18 through 45-year-olds) | 1 x 10^9 | 2687 | 93.5% [92.5%, 94.4%]
Difference in Seroconversion Ratesd,e |  |  | −3.1% [−6.7%, 0.4%]
a Data are derived from Study 1 (NCT02094586) and Study 4 (NCT02100631).
b N=number of subjects with analyzable samples at Day 1 and Day 11.
c CI=confidence interval.
d Seroconversion is defined as the percentages of subjects who had at least a 4-fold rise in vibriocidal antibody titer at 10 days post-vaccination compared to baseline.
e Pre-specified success criterion was that the lower bound of the two-sided 95% confidence interval on the difference in seroconversion rate (Study 4 minus Study 1) must be greater than -10 percentage points.

Vibriocidal Antibody Against Classical Ogawa, El Tor Inaba and El Tor Ogawa

V. cholerae serogroup O1 consists of four major subtypes: classical Inaba, classical Ogawa, El Tor Inaba and El Tor Ogawa. Serum vibriocidal antibody against the three types of V. cholerae not contained in the vaccine, namely classical Ogawa, El Tor Inaba and El Tor Ogawa, was also measured in Study 2 and Study 4. The percentages of vaccine recipients who seroconverted against each of the 4 major biotype/serotypes of V. cholerae serogroup O1 at 10 days post-vaccination (71.4% to 91.4%) are shown in Table 6.

Table 6: Seroconversion Rates 10 Days Post-Vaccination for the Four Major V. cholerae O1 Serogroup Biotypes and Serotypes in Studies 2 and 4 [Immunogenicity Evaluable Population]
Cholera Strain | Study 2a (18 through 45-year-olds) VAXCHORA Nb | Study 2a (18 through 45-year-olds) VAXCHORA %c [95% CId] | Study 4a (46 through 64-year-olds) VAXCHORA Nb | Study 4a (46 through 64-year-olds) VAXCHORA % [95% CI]
Classical Inabae | 93 | 90.3% [82.4%, 95.5%] | 291 | 90.4% [86.4%, 93.5%]
El Tor Inaba | 93 | 91.4% [83.8%, 96.2%] | 290 | 91.0% [87.1%, 94.1%]
Classical Ogawa | 93 | 87.1% [78.5%, 93.2%] | 291 | 73.2% [67.7%, 78.2%]
El Tor Ogawa | 93 | 89.2% [81.1%, 94.7%] | 290 | 71.4% [65.8%, 76.5%]
a Data are derived from Study 2 (NCT01895855) and Study 4 (NCT02100631).
b N=number of subjects with measurements at baseline and 10 days post-vaccination. One subject in Study 2 did not have a Day 11 measurement and was dropped from the analysis.
c Seroconversion is defined as the percentages of subjects who had at least a 4-fold rise in vibriocidal antibody titer at 10 days post-vaccination compared to the titer measured at baseline.
d CI=confidence interval.
e VAXCHORA contains the classical Inaba strain of V. cholerae O1.

Pediatric Trial - Vibriocidal Antibody Against the Vaccine Strain (classical Inaba)

The effectiveness of VAXCHORA for the pediatric population 2 through 17 years of age was demonstrated following comparison of the immune response to V. cholerae in children and adolescents to the immune response in adults following Vaxchora (immunobridging).

Study 5 was a randomized, double-blind, saline placebo-controlled safety and immunogenicity study conducted in the US. A total of 550 subjects 2 through 17 years of age not previously exposed to cholera were randomized 6:1 to receive one dose of VAXCHORA (1 x 10^9 CFU/dose) or placebo. Randomization was stratified by age into 3 age cohorts:

- Cohort 1: 12 to <18 years of age
- Cohort 2: 6 to <12 years of age
- Cohort 3: 2 to <6 years of age

In this study, classical Inaba vibriocidal antibody seroconversion rates at 10-days post-vaccination in children 2 through 17 years of age were compared to seroconversion rates in adults 18 through 45 years of age.

Immunobridging results for VAXCHORA, at 10 days post-vaccination, are shown in Table 7. The rate of seroconversion among pediatric placebo recipients was 1.5% [95% CI 0.3%, 8.0%] at 10 days post-vaccination.

Table 7: Vibriocidal Antibody Seroconversion Against Classical Inaba V. cholerae Vaccine Strain at 10 Days Post-Vaccination in Children aged 2 through 17 Years (Study 5) Compared to Adults 18 through 45 Years of Age (Study 1) [Bridging Analysis Populationb]
Study a | Dose/CFU | VAXCHORA Nb | VAXCHORA Seroconversion % [98.3% CIc]
Study 5 (2 through 17-year-olds) | 1 x 10^9 | 399 | 98.5% [96.2%, 99.4%]
Study 1 (18 through 45-year-olds) | 1 x 10^9 | 2687 | 93.5% [92.3%, 94.6%]
Difference in Seroconversion Ratesd,e |  |  | 5.0% [2.8%, 6.4%]
a Data are derived from Study 1 (NCT02094586) and Study 5 (NCT03220737).
b N=number of subjects with analyzable samples at Day 1 and Day 11 in the immunogenicity evaluable population.
c CI=confidence interval.
d Seroconversion is defined as the percentages of subjects who had at least a 4-fold rise in vibriocidal antibody titer at 10 days post-vaccination compared to baseline.
e Pre-specified success criterion was that the lower bound of the two-sided 96.7% confidence interval on the difference in seroconversion rate (Study 5 minus Study 1) must be greater than -10 percentage points. Co-primary criterion required the lower limit of the 98.3% CI to be ≥ 70% for the VAXCHORA group.

16 HOW SUPPLIED/STORAGE AND HANDLING

16.1 How Supplied

VAXCHORA is supplied as shown in Table 8. The contents of both packets are reconstituted with bottled water (purified, spring, or sparkling [carbonated]), to form one oral dose of the vaccine.

Table 8: VAXCHORA Product Presentation
Presentation | Carton NDC Number | Components
Single dose carton containing two packets | NDC 50632-015-02 | Buffer Component Packet NDC 50632-015-02 Active Component Packet NDC 50632-015-02

16.2 Storage and Handling

Store VAXCHORA buffer component and active component packets refrigerated at 36°F to 46°F (2°C to 8°C).

Protect from light and moisture.

Packages may be stored at 48°F to 77°F (9°C to 25°C) for no more than 24 hours prior to reconstitution.

17 PATIENT COUNSELING INFORMATION

Prior to administration of this vaccine, the health care professional should inform the individual of the following:

- Advise vaccine recipients to exercise caution regarding food and water consumed in cholera-affected areas, in accordance with the recommendations from the Centers for Disease Control and Prevention for the prevention of cholera in travelers.
- Educate vaccine recipients regarding the most common adverse reactions occurring within 7 days post-vaccination with VAXCHORA (tiredness, headache, abdominal pain, nausea/vomiting, lack of appetite, and diarrhea).
- Inform vaccine recipients that VAXCHORA is a live attenuated vaccine and has the potential for transmission of the vaccine strain to close contacts (e.g., household contacts). For at least 14 days following vaccination with VAXCHORA, vaccine recipients should wash their hands thoroughly after using the bathroom and before preparing or handling food.
- Instruct vaccine recipients to report adverse reactions to their healthcare provider.

VAXCHORA® is a registered trademark of Bavarian Nordic A/S

US License No. 2096

Manufactured by: Bavarian Nordic A/S, Philip Heymans Alle 3, 2900 Hellerup, Denmark

© 2023 Bavarian Nordic A/S. All rights reserved.

PRINCIPAL DISPLAY PANEL - Carton

Carton

NDC 50632-015-02

STORE REFRIGERATED
Use After Reconstitution

Cholera Vaccine, Live, Oral
Vaxchora®

Contents: Single-dose Active Packet (4x10^8 to 2x10^9 CFU of
Vibrio cholerae CVD 103-HgR) and Single-dose Buffer Packet.

Prior to administration, reconstitute Buffer in 100 mL of
bottled water (purified, spring or sparkling). For children
under 6 years of age only, discard half the buffer solution.
After reconstitution, then add Active.
See package insert.

Cholera Vaccine, Live, Oral
Vaxchora®

Bavarian Nordic A/S, Denmark
BAVARIAN NORDIC

Cholera Vaccine, Live Oral
Vaxchora®

Live vaccine for oral, active immunization against cholera
Store at 36 °F to 46 °F (2 °C to 8 °C)

Administration and dosage: see package insert

Manufactured by:
Bavarian Nordic A/S
Philip Heymans Alle 3
2900 Hellerup, Denmark

US License No. 2096

Rx ONLY

GTIN:
S/N:
EXP:
LOT:

PRINCIPAL DISPLAY PANEL - Buffer and Active Packets

BUFFER COMPONENT
OF VAXCHORA®
(Cholera Vaccine, Live, Oral)

1

Packet 1 of 2. USE FIRST.

Contents (Single-Dose): Buffer

Directions: Add entire contents
of Packet 1 to 100 mL of bottled
water (purified, spring or sparkling)
in disposable cup, then stir.
For children under 6 years of age
only, discard half the buffer solution.
Go to Packet 2. See package insert.

Rx Only - For Oral Administration

EXP: LOT:

NDC 50632-015-02

Bavarian Nordic A/S
US License No. 2096

ACTIVE COMPONENT
of VAXCHORA®
(Cholera Vaccine, Live, Oral)

2

Packet 2 of 2. USE LAST.

Contents (Single-Dose):
4x10^8 to 2x10^9 CFU of
lyophilized Vibrio cholerae
CVD 103-HgR.

Directions: Add contents of Packet 2
to cup and stir to create vaccine. See
package insert.

Rx Only - For Oral Administration

EXP: LOT:

NDC 50632-015-02

Bavarian Nordic A/S
US License No. 2096